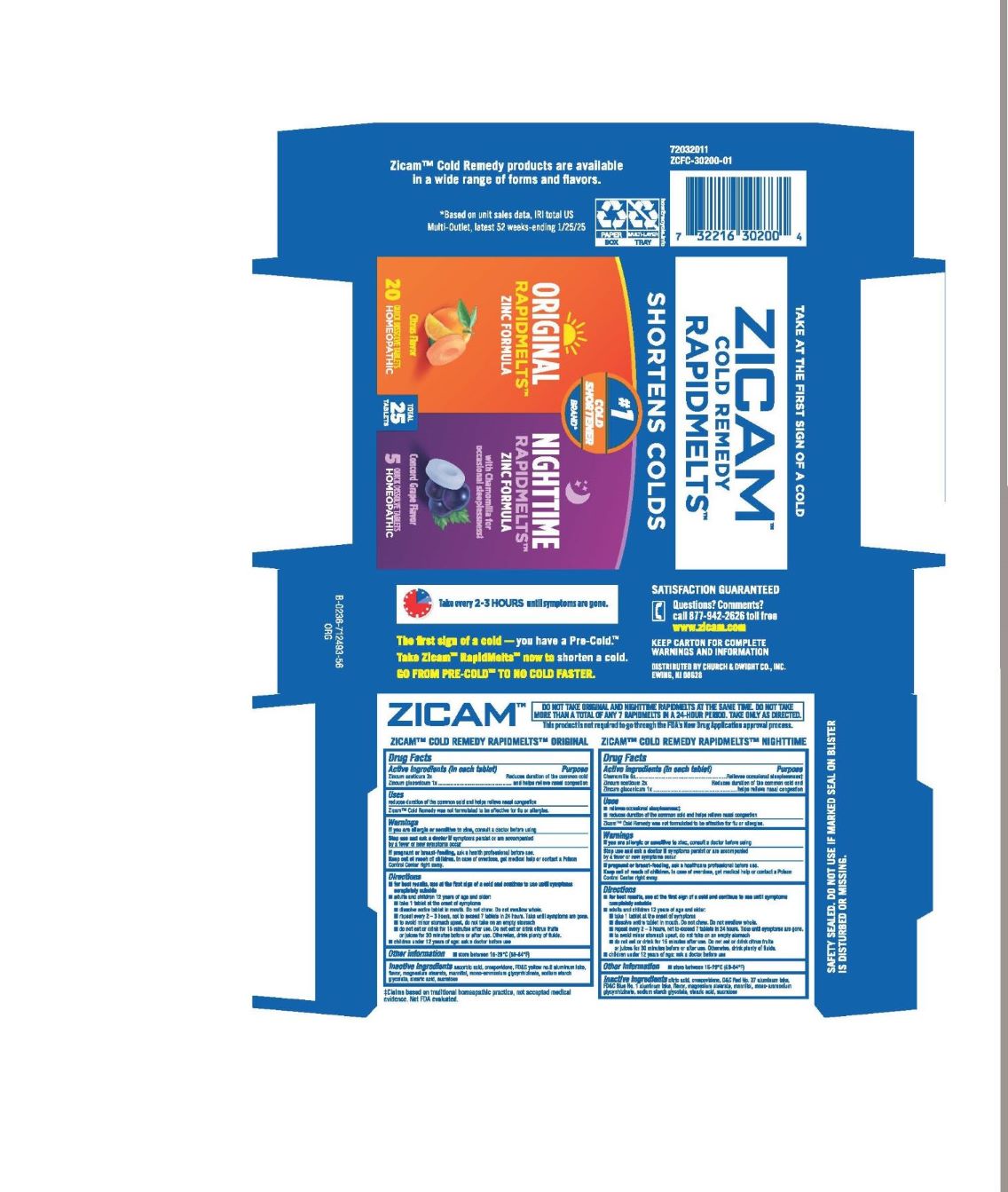 DRUG LABEL: Zicam
NDC: 10237-480 | Form: KIT | Route: ORAL
Manufacturer: Church & Dwight Co., Inc.
Category: homeopathic | Type: HUMAN OTC DRUG LABEL
Date: 20250701

ACTIVE INGREDIENTS: ZINC ACETATE ANHYDROUS 2 [hp_X]/1 1; ZINC GLUCONATE 1 [hp_X]/1 1; ZINC ACETATE ANHYDROUS 2 [hp_X]/1 1; ZINC GLUCONATE 1 [hp_X]/1 1; MATRICARIA CHAMOMILLA 5 [hp_X]/1 1
INACTIVE INGREDIENTS: ALUMINUM OXIDE; MAGNESIUM STEARATE; MANNITOL; AMMONIUM GLYCYRRHIZATE; FD&C YELLOW NO. 6; STEARIC ACID; CROSPOVIDONE (15 MPA.S AT 5%); ASCORBIC ACID; SUCRALOSE; SODIUM STARCH GLYCOLATE TYPE A POTATO; CROSPOVIDONE (15 MPA.S AT 5%); MANNITOL; AMMONIUM GLYCYRRHIZATE; ANHYDROUS CITRIC ACID; MAGNESIUM STEARATE; D&C RED NO. 27 ALUMINUM LAKE; FD&C BLUE NO. 1 ALUMINUM LAKE; SODIUM STARCH GLYCOLATE TYPE A POTATO; STEARIC ACID; SUCRALOSE

Zicam Cold Remedy RapidMelts Original and Nighttime Convenience Pack

DRUG FACTS

Zicam Cold Remedy Rapidmelts Original

Active ingredients (in each tablet)

Zincum aceticum 2x
Zincum gluconicum 1x

Purpose

Reduces duration of the common cold and helps relieve nasal congestion

Uses

Reduces duration of the common cold and helps relieve nasal congestion

Zicam Cold Remedy ws not formulated to be effective for flu or allergies.

Warnings

ASK DOCTOR

If you are allergic or sensitive to zinc, consult a doctor before using

Stop use and ask a doctor if symptoms persist or are accompanied by a fever or new symptoms occur

PREGNANCY OR BREAST FEEDING

If pregnant or breast-feeding, ask a health professional before use.

Keep out of reach of children. In case of overdose, get medical help or contact a Poison Control Center right away.

Directions

- for best results, use at the first sign of a cold and continue to use until symptoms completely subside
- adults and children 12 years of age and older:
  - take 1 tablet at the onset of symptoms
  - dissolve entire tablet in mouth. Do not chew. Do not swallow whole.
  - repeat every 2–3 hours, not to exceed 7 tablets in 24 hours. Take until symptoms are gone.
  - to avoid minor stomach upset, do not take on an empty stomach
  - do not eat or drink for 15 minutes after use. Do not eat or drink citrus fruits or juices for 30 minutes before or after use. Otherwise, drink plenty of fluids.
- children under 12 years of age: ask a doctor before use

DO NOT TAKE ORIGINAL AND NIGHTTIME RAPIDMELTS AT THE SAME TIME, DO NOT TAKE MORE THAN A TOTAL OF ANY 7 RAPIDMELTS IN A 24-HOUR PERIOD. TAKE ONLY AS DIRECTED.

Other Information

- store between 15-29°C (59-84°F)
- KEEP CARTON FOR COMPLETE WARNINGS AND INFORMATION

Inactive Ingredients

ascorbic acid, crospovidone, FD&C yellow no. 6 aluminum lake, magnesium stearate, mannitol, mono-ammonium glycyrrhizinate, natural and artificial flavor, sodium starch glycolate, stearic acid, sucralose

Questions? Comments? Side Effects?

call 877-942-2626 toll free

www.zicam.com

DRUG FACTS

Zicam Cold Remedy Rapidmelts Nighttime

Active Ingredients (in each tablet)

Chamomilla 5x

Zincum aceticum 2x

Zincum gluconicum 1x

Purpose

Relieves occasional sleeplessness

Reduces duration of the common cold and helps relieve nasal congestion

Uses

Relieves occasional sleeplessness

Reduces duration of the common cold and helps relieve nasal congestion

Zicam Cold Remedy was not formulated to be effective for flu or allergies.

Warnings

ASK DOCTOR

If you are allergic or sensitive to zinc, consult a doctor before using

Stop use and ask a doctor if symptoms persist or are accompanied by a fever or new symptoms occur

PREGNANCY OR BREAST FEEDING

If pregnant or breast-feeding, ask a health professional before use.

Keep out of reach of children. In case of overdose, get medical help or contact a Poison Control Center right away.

Directions

- for best results, use at the first sign of a cold and continue to use until symptoms completely subside
- adults and children 12 years of age and older:
  - take 1 tablet at the onset of symptoms
  - dissolve entire tablet in mouth. Do not chew. Do not swallow whole.
  - repeat every 2–3 hours, not to exceed 7 tablets in 24 hours. Take until symptoms are gone.
  - to avoid minor stomach upset, do not take on an empty stomach
  - do not eat or drink for 15 minutes after use. Do not eat or drink citrus fruits or juices for 30 minutes before or after use. Otherwise, drink plenty of fluids.
- children under 12 years of age: ask a doctor before use

DO NOT TAKE ORIGINAL AND NIGHTTIME RAPIDMELTS AT THE SAME TIME, DO NOT TAKE MORE THAN A TOTAL OF ANY 7 RAPIDMELTS IN A 24-HOUR PERIOD. TAKE ONLY AS DIRECTED.

Other Information

- store between 15-29°C (59-84°F)
- KEEP CARTON FOR COMPLETE WARNINGS AND INFORMATION.

Inactive Ingredients

citric acid, crospovidone, D&C red no. 27 aluminum lake, FD&C Blue No. 1 aluminum lake, flavor, magnesium stearate, mannitol, mono-ammonium glycyrrhizinate, sodium starch glycolate, stearic acid, sucralose

Questions? Comments? Side Effects?

call 877-942-2626 toll free

www.zicam.com

PRINCIPAL DISPLAY PANEL

ZICAM COLD REMEDY RAPIDMELTS

SHORTENS COLDS

#1 COLD SHORTENER BRAND

ORIGINAL RAPIDMELTS ZINC FORMULA

Citrus Flavor

20 QUICK DISSOLVE TABLETS

HOMEOPATHIC

NIGHTTIME RAPIDMELTS ZINC FORMULA

with Chamomilla for occasional sleeplessness

Concord Grape Flavor
5 QUICK DISSOLVE TABLETS
HOMEOPATHIC

25 TABLETS TOTAL